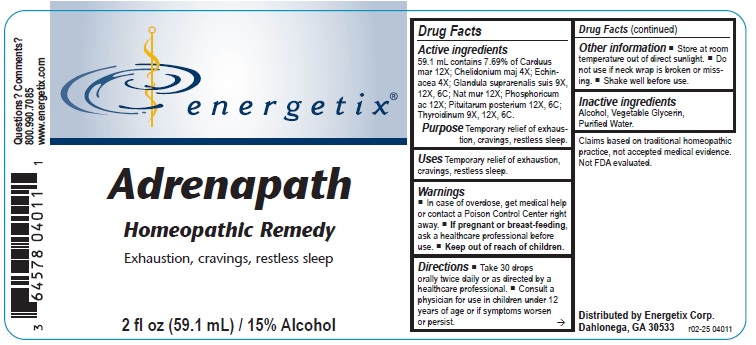 DRUG LABEL: Adrenapath
NDC: 64578-0096 | Form: LIQUID
Manufacturer: Energetix Corporation
Category: homeopathic | Type: HUMAN OTC DRUG LABEL
Date: 20250711

ACTIVE INGREDIENTS: MILK THISTLE 12 [hp_X]/1 mL; CHELIDONIUM MAJUS 4 [hp_X]/1 mL; ECHINACEA ANGUSTIFOLIA 4 [hp_X]/1 mL; SUS SCROFA ADRENAL GLAND 9 [hp_X]/1 mL; SODIUM CHLORIDE 12 [hp_X]/1 mL; PHOSPHORIC ACID 12 [hp_X]/1 mL; BOS TAURUS PITUITARY GLAND 12 [hp_X]/1 mL; THYROID, BOVINE 9 [hp_X]/1 mL
INACTIVE INGREDIENTS: WATER; ALCOHOL; GLYCERIN

Adrenapath

Active ingredients

59.1 mL contains 7.69% of Carduus mar 12X; Chelidonium maj 4X; Echinacea 4X; Glandula suprarenalis suis 9X, 12X, 6C; Nat mur 12X; Phosphoricum ac 12X; Pituitarum posterium 12X, 6C; Thyroidinum 9X, 12X, 6C.

Claims based on traditional homeopathic practice, not accepted medical evidence. Not FDA evaluated.

Uses

Temporary relief of exhaustion, cravings, restless sleep.

Warnings

- In case of overdose, get medical help or contact a Poison Control Center right away.
- If pregnant or breast-feeding, ask a healthcare professional before use.

- Keep out of reach of children.

Directions

- Take 30 drops orally twice daily or as directed by a healthcare professional.
- Consult a physician for use in children under 12 years of age or if symptoms worsen or persist.

Other information

- Store at room temperature out of direct sunlight.
- Do not use if neck wrap is broken or missing.
- Shake well before use.

Inactive ingredients

Alcohol, Vegetable Glycerin, Purified Water.

QUESTIONS

Distributed by Energetix Corp.

Dahlonega, GA 30533

Questions? Comments?

800.990.7085

www.energetix.com

PACKAGE LABEL

energetix

Adrenapath

Homeopathic Remedy

Exhaustion, cravings, restless sleep

2 fl oz (59.1 mL) / 15% Alcohol

Purpose Temporary relief of exhaustion, cravings, restless sleep.